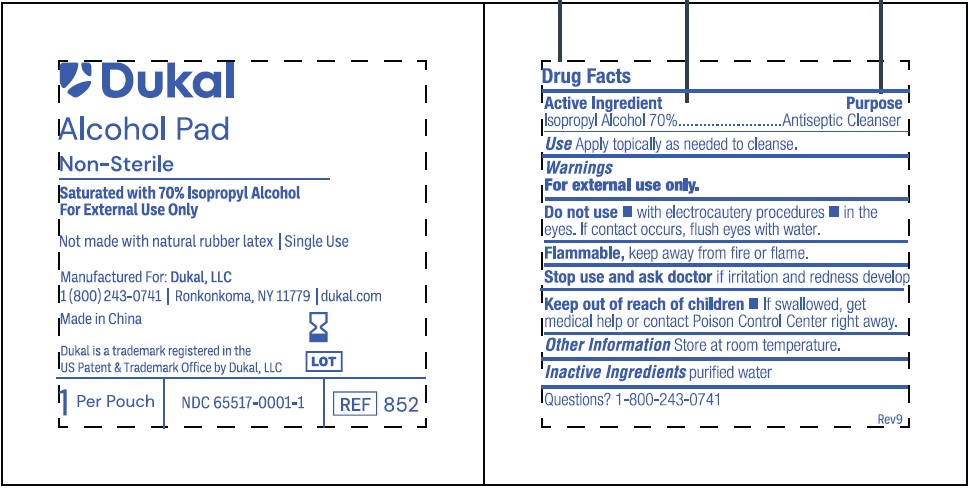 DRUG LABEL: Dukal Alcohol Prep Pad
NDC: 65517-0001 | Form: SWAB
Manufacturer: Dukal LLC
Category: otc | Type: HUMAN OTC DRUG LABEL
Date: 20251119

ACTIVE INGREDIENTS: ISOPROPYL ALCOHOL 0.7 mL/1 mL
INACTIVE INGREDIENTS: WATER

65517-0001 - Alcohol Prep Pads

Drug Facts

Active Ingredients

Isopropyl Alcohol 70%

Purpose

Antiseptic Cleanser

INDICATIONS AND USAGE

Apply topically as needed to cleanse

Indications & Usage Section

Updated to match the label claim

Warnings

- For External Use Only
- Flammable, Keep away from fire or flame

Do Not Use

- with electrocautery procedures
- In the Eyes. If contact occurs, flush eyes with water

Stop Use

If irritation and redness develop. If condition persists, consult your health care practitioner.

Keep out of reach of children

If swallowed, get medical help or contact a Poison Control Center right away.

Directions

Wipe injection site vigorously and discard.

Other Information

Store at Room Temperature 15 - 30 C (59 - 86 F)

Inactive Ingredient

purified water

PACKAGE LABEL

Dukal

Alcohol Pad

Non-Sterile

Saturated with 70% Isopropyl Alcohol

For External Use Only

Not made with natural rubber latex / Single Use

Manufactured For: Dukal, LLC

1(800)243-0741 /Ronkonkoma, NY 11779 / dukal.com

Made in China

Dukal is a trademark registered in the

US Patent & Trademark Office by Dukal, LLC

1 Per Pouch / NDC 65517-0001-1 / REF 852